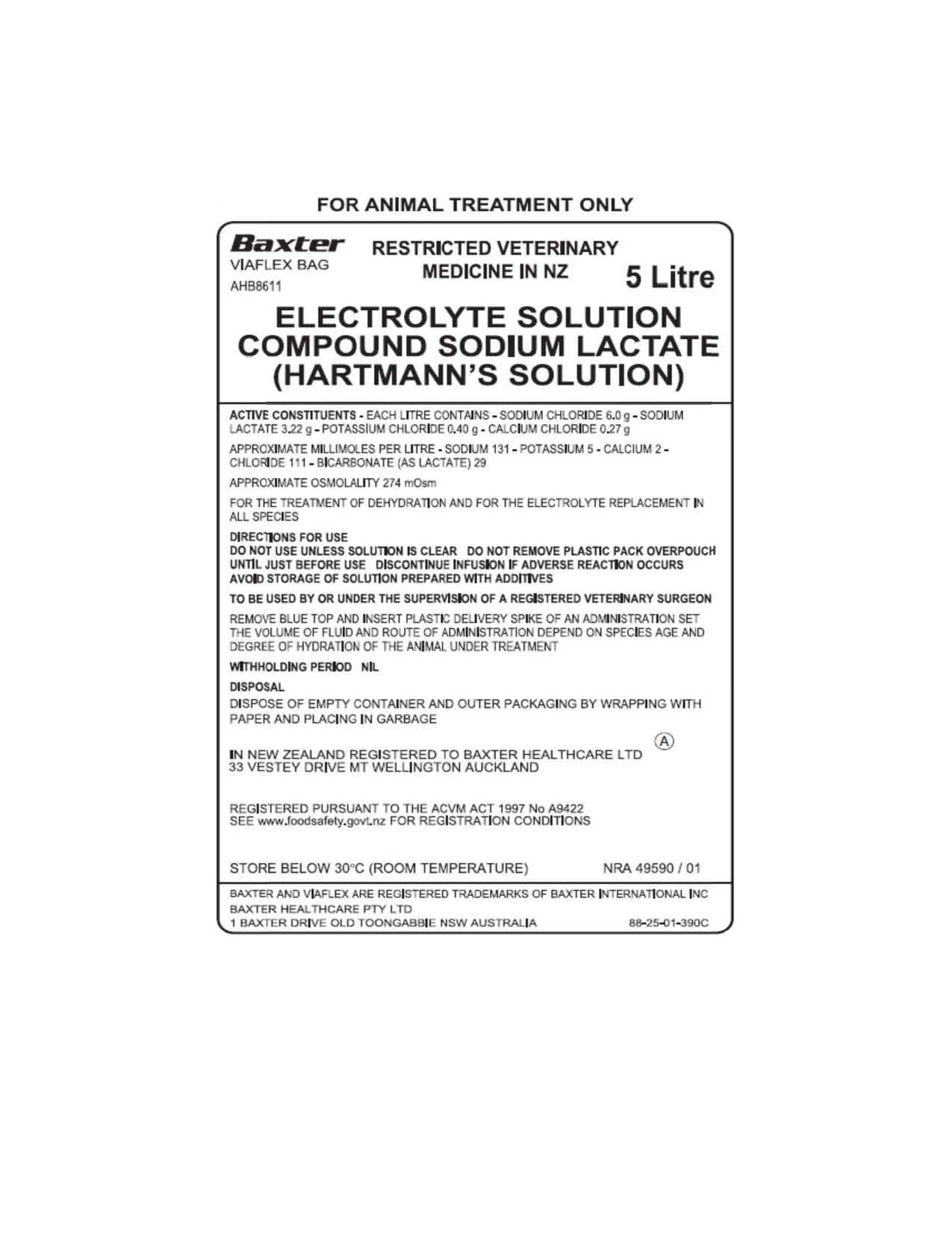 DRUG LABEL: COMPOUND SODIUM LACTATE
NDC: 86046-8611 | Form: INJECTION, SOLUTION
Manufacturer: Baxter Healthcare Pty Ltd
Category: animal | Type: PRESCRIPTION ANIMAL DRUG LABEL
Date: 20150330

ACTIVE INGREDIENTS: SODIUM CHLORIDE 6 g/1 L; SODIUM LACTATE 3.22 g/1 L; POTASSIUM CHLORIDE 400 mg/1 L; CALCIUM CHLORIDE 270 mg/1 L
INACTIVE INGREDIENTS: WATER

Electrolyte Solution
COMPOUND SODIUM LACTATE (HARTMANN'S SOLUTION) 5 L

For Animal Use Only

Description

COMPOUND SODIUM LACTATE (HARTMANN'S SOLUTION) Injection is a sterile, nonpyrogenic solution for fluid and electrolyte replenishment. It is supplied in single dose VIAFLEX plastic containers for intravenous administration. It contains no antimicrobial agents. Any unused portion should be discarded.

The composition and ionic concentration of COMPOUND SODIUM LACTATE (HARTMANN'S SOLUTION) Injection are shown in Tables 1 and 2 below.

Table 1 - Composition (g/L)
Sodium chloride | 6
Sodium lactate | 3.22
Potassium chloride | 0.4
Calcium chloride | 0.27

Table 2 - Ionic concentration (mEq/L)
Sodium | 131
Potassium | 5
Calcium | 4
Chloride | 111
Lactate | 29

Indications

COMPOUND SODIUM LACTATE (HARTMANN'S SOLUTION) Injection is indicated as a source of water and electrolytes or as an alkalinizing agent.

Warnings

COMPOUND SODIUM LACTATE (HARTMANN'S SOLUTION) Injection should be used with great care, if at all, in animals with congestive heart failure, severe renal insufficiency, and in clinical states in which there exists edema with sodium retention.
COMPOUND SODIUM LACTATE (HARTMANN'S SOLUTION) Injection should be used with great care, if at all, in animals with hyperkalemia, severe renal failure, and in conditions in which potassium retention is present.
COMPOUND SODIUM LACTATE (HARTMANN'S SOLUTION) Injection should be used with great care in animals with metabolic or respiratory alkalosis. The administration of lactate ions should be done with great care in those conditions in which there is an increased level or an impaired utilization of these ions, such as severe hepatic insufficiency.
COMPOUND SODIUM LACTATE (HARTMANN'S SOLUTION) Injection should not be administered simultaneously with blood through the same administration set because of the likelihood of coagulation.
The intravenous administration of COMPOUND SODIUM LACTATE (HARTMANN'S SOLUTION) Injection can cause fluid and/or solute overloading resulting in dilution of serum electrolyte concentrations, overhydration, congested states, or pulmonary edema. The risk of dilutional states is inversely proportional to the electrolyte concentrations of the injections. The risk of solute overload causing congested states with peripheral and pulmonary edema is directly proportional to the electrolyte concentrations of the injections.
In patients with diminished renal function, administration of COMPOUND SODIUM LACTATE (HARTMANN'S SOLUTION) Injection may result in sodium or potassium retention.
COMPOUND SODIUM LACTATE (HARTMANN'S SOLUTION) Injection is not for use in the treatment of lactic acidosis.

Precautions

Clinical evaluation and periodic laboratory determinations are necessary to monitor changes in fluid balance, electrolyte concentrations, and acid base balance during prolonged parenteral therapy or whenever the condition of the animal warrants such evaluation.
COMPOUND SODIUM LACTATE (HARTMANN'S SOLUTION) Injection must be used with caution. Excess administration may result in metabolic alkalosis.
Caution must be exercised in the administration of COMPOUND SODIUM LACTATE (HARTMANN'S SOLUTION) Injection to patients receiving corticosteroids or corticotropin.
Do not administer unless solution is clear and seal is intact.
Reactions which may occur because of the solution or the technique of administration include febrile response, infection at the site of injection, venous thrombosis or phlebitis extending from the site of injection, extravasation, and hypervolemia.
If an adverse reaction does occur, discontinue the infusion, evaluate the animal, institute appropriate therapeutic countermeasures, and save the remainder of the fluid for examination if deemed necessary.

Adverse Reactions

Reactions which may occur because of the solution or the technique of administration include febrile response, infection at the site of injection, venous thrombosis or phlebitis extending from the site of injection, extravasation, and hypervolemia. If an adverse reaction does occur, discontinue the infusion, evaluate the animal, institute appropriate therapeutic countermeasures, and save the remainder of the fluid for examination if deemed necessary.

Dosage and Administration

As directed by a veterinarian. Dosage is dependent upon the age, weight and clinical condition of the animal as well as laboratory determinations.
Parenteral drug products should be inspected visually for particulate matter and discoloration prior to administration whenever solution and container permit.
All injections in plastic containers are intended for intravenous administration using sterile equipment.
Additives may be incompatible. Complete information is not available. Those additives known to be incompatible should not be used. Consult with pharmacist, if available. If, in the informed judgment of the veterinarian, it is deemed advisable to introduce additives, use aseptic technique. Mix thoroughly when additives have been introduced. Do not store solutions containing additives.

OverDosage

In an event of overhydration or solute overload, re-evaluate the animal and institute appropriate corrective measures. See Warnings, Precautions and Adverse Reactions.

How Supplied

COMPOUND SODIUM LACTATE (HARTMANN'S SOLUTION) Injection is supplied in following pack size:

- 5L solution in single dose VIAFLEX plastic containers.

Exposure of pharmaceutical products to heat should be minimized.
Avoid excessive heat. It is recommended the product be stored at room temperature below 30°C/86ºF.

Directions for Use of VIAFLEX plastic container

To Open
Tear overwrap down side at slit and remove solution container. Some opacity of the plastic due to moisture absorption during the sterilization process may be observed. This is normal and does not affect the solution quality or safety. The opacity will diminish gradually. Check for minute leaks by squeezing inner bag firmly. If leaks are found, discard solution as sterility may be impaired. If supplemental medication is desired, follow directions below.

Preparation for Administration
1. Suspend container from eyelet support.
2. Remove plastic protector from outlet port at bottom of container.
3. Attach administration set.

To Add Medication
WARNING: Additives may be incompatible.

To add medication before solution administration
1. Prepare medication site.
2. Using syringe with 19 to 22 gauge needle, puncture medication port and inject.
3. Mix solution and medication thoroughly. For high density medication such as potassium chloride, squeeze ports while ports are upright and mix thoroughly.

To add medication during solution administration
1. Close clamp on the set.
2. Prepare medication site.
3. Using syringe with 19 to 22 gauge needle, puncture resealable medication port and inject.
4. Remove container from IV pole and/or turn to an upright position.
5. Evacuate both ports by squeezing them while container is in the upright position.
6. Mix solution and medication thoroughly.
7. Return container to in use position and continue administration.

CAUTION: Federal law restricts this drug to use by or on the order of a licensed veterinarian.